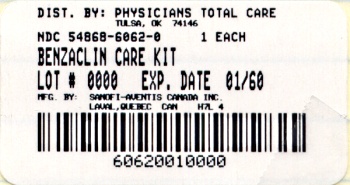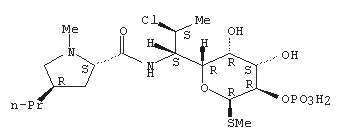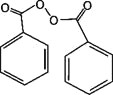 DRUG LABEL: BENZACLIN
NDC: 54868-6062 | Form: GEL
Manufacturer: Physicians Total Care, Inc.
Category: prescription | Type: HUMAN PRESCRIPTION DRUG LABEL
Date: 20111227

ACTIVE INGREDIENTS: clindamycin phosphate 10 mg/1 g; benzoyl peroxide 50 mg/1 g
INACTIVE INGREDIENTS: sodium hydroxide; water

Topical Gel: clindamycin (1%) as clindamycin phosphate, benzoyl peroxide (5%)
For Dermatological Use Only - Not for Ophthalmic Use
*SAMPLE. NO RECONSTITUTION NECESSARY*

DESCRIPTION

BenzaClin® Topical Gel contains clindamycin phosphate, (7(S)-chloro-7-deoxylincomycin-2-phosphate). Clindamycin phosphate is a water soluble ester of the semi-synthetic antibiotic produced by a 7(S)-chloro-substitution of the 7(R)-hydroxyl group of the parent antibiotic lincomycin.

Chemically, clindamycin phosphate is (C18H34ClN2O8PS). The structural formula for clindamycin is represented below:

Clindamycin phosphate has molecular weight of 504.97 and its chemical name is Methyl 7-chloro-6,7,8-trideoxy-6-(1-methyl-trans-4-propyl-L-2-pyrrolidinecarboxamido)-1-thio-L-threo-alpha-D-galacto-octopyranoside 2-(dihydrogen phosphate).

BenzaClin Topical Gel also contains benzoyl peroxide, for topical use.
Chemically, benzoyl peroxide is (C14H10O4). It has the following structural formula:

Benzoyl peroxide has a molecular weight of 242.23.

Each gram of BenzaClin Topical Gel contains, as dispensed, 10 mg (1%) clindamycin as phosphate and 50 mg (5%) benzoyl peroxide in a base of carbomer, sodium hydroxide, dioctyl sodium sulfosuccinate, and purified water.

CLINICAL PHARMACOLOGY

An in vitro percutaneous penetration study comparing BenzaClin Topical Gel and topical 1% clindamycin gel alone, demonstrated there was no statistical difference in penetration between the two drugs. Mean systemic bioavailability of topical clindamycin in BenzaClin Topical Gel is suggested to be less than 1%.

Benzoyl peroxide has been shown to be absorbed by the skin where it is converted to benzoic acid. Less than 2% of the dose enters systemic circulation as benzoic acid. It is suggested that the lipophilic nature of benzoyl peroxide acts to concentrate the compound into the lipid-rich sebaceous follicle.

Microbiology

The clindamycin and benzoyl peroxide components individually have been shown to have in vitro activity against Propionibacterium acnes an organism which has been associated with acne vulgaris; however, the clinical significance of this activity against P. acnes was not examined in clinical trials with this product.

CLINICAL STUDIES

In two adequate and well controlled clinical studies of 758 patients, 214 used BenzaClin, 210 used benzoyl peroxide, 168 used clindamycin, and 166 used vehicle. BenzaClin applied twice daily for 10 weeks was significantly more effective than vehicle in the treatment of moderate to moderately severe facial acne vulgaris. Patients were evaluated and acne lesions counted at each clinical visit; weeks 2, 4, 6, 8 and 10. The primary efficacy measures were the lesion counts and the investigator's global assessment evaluated at week 10. Patients were instructed to wash the face with a mild soap, using only the hands. Fifteen minutes after the face was thoroughly dry, application was made to the entire face. Non-medicated make-up could be applied at one hour after the BenzaClin application. If a moisturizer was required, the patients were provided a moisturizer to be used as needed. Patients were instructed to avoid sun exposure. Percent reductions in lesion counts after treatment for 10 weeks in these two studies are shown below:

Study 1
BenzaClin | Benzoyl peroxide | Clindamycin | Vehicle
n=120 | n=120 | n=120 | n=120
Mean percent reduction in inflammatory lesion counts
46% | 32% | 16% | + 3%
Mean percent reduction in non-inflammatory lesion counts
22% | 22% | 9% | +1%
Mean percent reduction in total lesion counts
36% | 28% | 15% | 0.2%

Study 2
BenzaClin | Benzoyl peroxide | Clindamycin | Vehicle
n=95 | n=95 | n=49 | n=48
Mean percent reduction in inflammatory lesion counts
63% | 53% | 45% | 42%
Mean percent reduction in non-inflammatory lesion counts
54% | 50% | 39% | 36%
Mean percent reduction in total lesion counts
58% | 52% | 42% | 39%

The BenzaClin group showed greater overall improvement than the benzoyl peroxide, clindamycin and vehicle groups as rated by the investigator.

INDICATIONS AND USAGE

BenzaClin Topical Gel is indicated for the topical treatment of acne vulgaris.

CONTRAINDICATIONS

BenzaClin Topical Gel is contraindicated in those individuals who have shown hypersensitivity to any of its components or to lincomycin. It is also contraindicated in those having a history of regional enteritis, ulcerative colitis, or antibiotic-associated colitis.

WARNINGS

ORALLY AND PARENTERALLY ADMINISTERED CLINDAMYCIN HAS BEEN ASSOCIATED WITH SEVERE COLITIS WHICH MAY RESULT IN PATIENT DEATH. USE OF THE TOPICAL FORMULATION OF CLINDAMYCIN RESULTS IN ABSORPTION OF THE ANTIBIOTIC FROM THE SKIN SURFACE. DIARRHEA, BLOODY DIARRHEA, AND COLITIS (INCLUDING PSEUDOMEMBRANOUS COLITIS) HAVE BEEN REPORTED WITH THE USE OF TOPICAL AND SYSTEMIC CLINDAMYCIN. STUDIES INDICATE A TOXIN(S) PRODUCED BY CLOSTRIDIA IS ONE PRIMARY CAUSE OF ANTIBIOTIC-ASSOCIATED COLITIS. THE COLITIS IS USUALLY CHARACTERIZED BY SEVERE PERSISTENT DIARRHEA AND SEVERE ABDOMINAL CRAMPS AND MAY BE ASSOCIATED WITH THE PASSAGE OF BLOOD AND MUCUS. ENDOSCOPIC EXAMINATION MAY REVEAL PSEUDOMEMBRANOUS COLITIS. STOOL CULTURE FOR Clostridium Difficile AND STOOL ASSAY FOR C. difficile TOXIN MAY BE HELPFUL DIAGNOSTICALLY. WHEN SIGNIFICANT DIARRHEA OCCURS, THE DRUG SHOULD BE DISCONTINUED. LARGE BOWEL ENDOSCOPY SHOULD BE CONSIDERED TO ESTABLISH A DEFINITIVE DIAGNOSIS IN CASES OF SEVERE DIARRHEA. ANTIPERISTALTIC AGENTS SUCH AS OPIATES AND DIPHENOXYLATE WITH ATROPINE MAY PROLONG AND/OR WORSEN THE CONDITION. DIARRHEA, COLITIS, AND PSEUDOMEMBRANOUS COLITIS HAVE BEEN OBSERVED TO BEGIN UP TO SEVERAL WEEKS FOLLOWING CESSATION OF ORAL AND PARENTERAL THERAPY WITH CLINDAMYCIN.

Mild cases of pseudomembranous colitis usually respond to drug discontinuation alone. In moderate to severe cases, consideration should be given to management with fluids and electrolytes, protein supplementation and treatment with an antibacterial drug clinically effective against C. difficile colitis.

PRECAUTIONS

General

For dermatological use only; not for ophthalmic use. Concomitant topical acne therapy should be used with caution because a possible cumulative irritancy effect may occur, especially with the use of peeling, desquamating, or abrasive agents.

The use of antibiotic agents may be associated with the overgrowth of nonsusceptible organisms including fungi. If this occurs, discontinue use of this medication and take appropriate measures.

Avoid contact with eyes and mucous membranes.

Clindamycin and erythromycin containing products should not be used in combination. In vitro studies have shown antagonism between these two antimicrobials. The clinical significance of this in vitro antagonism is not known.

Information for Patients

Patients using BenzaClin Topical Gel should receive the following information and instructions:

1. BenzaClin Topical Gel is to be used as directed by the physician. It is for external use only. Avoid contact with eyes, and inside the nose, mouth, and all mucous membranes, as this product may be irritating.
2. This medication should not be used for any disorder other than that for which it was prescribed.
3. Patients should not use any other topical acne preparation unless otherwise directed by physician.
4. Patients should minimize or avoid exposure to natural or artificial sunlight (tanning beds or UVA/B treatment) while using BenzaClin Topical Gel. To minimize exposure to sunlight, a wide-brimmed hat or other protective clothing should be worn, and a sunscreen with SPF 15 rating or higher should be used.
5. Patients who develop allergic symptoms such as severe swelling or shortness of breath should discontinue BenzaClin Topical Gel and contact their physician immediately. In addition, patients should report any signs of local adverse reactions to their physician.
6. BenzaClin Topical Gel may bleach hair or colored fabric.
7. BenzaClin Topical Gel can be stored at room temperature 25°C (77°F). Do not freeze. Discard any unused product after expiration date on sample.
8. Before applying BenzaClin Topical Gel to affected areas wash the skin gently, then rinse with warm water and pat dry.

Carcinogenesis, Mutagenesis, Impairment of Fertility

Benzoyl peroxide has been shown to be a tumor promoter and progression agent in a number of animal studies. The clinical significance of this is unknown.

Benzoyl peroxide in acetone at doses of 5 and 10 mg administered twice per week induced skin tumors in transgenic Tg.AC mice in a study using 20 weeks of topical treatment.

In a 52 week dermal photocarcinogenicity study in hairless mice, the median time to onset of skin tumor formation was decreased and the number of tumors per mouse increased following chronic concurrent topical administration of BenzaClin Topical Gel with exposure to ultraviolet radiation (40 weeks of treatment followed by 12 weeks of observation).

In a 2-year dermal carcinogenicity study in rats, treatment with BenzaClin Topical Gel at doses of 100, 500 and 2000 mg/kg/day caused a dose-dependent increase in the incidence of keratoacanthoma at the treated skin site of male rats. The incidence of keratoacanthoma at the treated site of males treated with 2000 mg/kg/day (8 times the highest recommended adult human dose of 2.5 g BenzaClin Topical Gel, based on mg/m^2) was statistically significantly higher than that in the sham- and vehicle-controls.

Genotoxicity studies were not conducted with BenzaClin Topical Gel. Clindamycin phosphate was not genotoxic in Salmonella typhimurium or in a rat micronucleus test. Clindamycin phosphate sulfoxide, an oxidative degradation product of clindamycin phosphate and benzoyl peroxide, was not clastogenic in a mouse micronucleus test. Benzoyl peroxide has been found to cause DNA strand breaks in a variety of mammalian cell types, to be mutagenic in S. typhimurium tests by some but not all investigators, and to cause sister chromatid exchanges in Chinese hamster ovary cells. Studies have not been performed with BenzaClin Topical Gel or benzoyl peroxide to evaluate the effect on fertility. Fertility studies in rats treated orally with up to 300 mg/kg/day of clindamycin (approximately 120 times the amount of clindamycin in the highest recommended adult human dose of 2.5 g BenzaClin Topical Gel, based on mg/m^2) revealed no effects on fertility or mating ability.

Pregnancy

Teratogenic Effects

Pregnancy Category C

Animal reproductive/developmental toxicity studies have not been conducted with BenzaClin Topical Gel or benzoyl peroxide. Developmental toxicity studies performed in rats and mice using oral doses of clindamycin up to 600 mg/kg/day (240 and 120 times amount of clindamycin in the highest recommended adult human dose based on mg/m^2, respectively) or subcutaneous doses of clindamycin up to 250 mg/kg/day (100 and 50 times the amount of clindamycin in the highest recommended adult human dose based on mg/m^2, respectively) revealed no evidence of teratogenicity.

There are no well-controlled trials in pregnant women treated with BenzaClin Topical Gel. It also is not known whether BenzaClin Topical Gel can cause fetal harm when administered to a pregnant woman.

Nursing Women

It is not known whether BenzaClin Topical Gel is excreted in human milk after topical application. However, orally and parenterally administered clindamycin has been reported to appear in breast milk. Because of the potential for serious adverse reactions in nursing infants, a decision should be made whether to discontinue nursing or to discontinue the drug, taking into account the importance of the drug to the mother.

Pediatric Use

Safety and effectiveness of this product in pediatric patients below the age of 12 have not been established.

ADVERSE REACTIONS

During clinical trials, the most frequently reported adverse event in the BenzaClin treatment group was dry skin (12%). The Table below lists local adverse events reported by at least 1% of patients in the BenzaClin and vehicle groups.

Local Adverse Events - all causalities in >/= 1% of patients
 | BenzaClin | Vehicle
 | n = 420 | n = 168
Application site reaction | 13 (3%) | 1 (<1%)
Dry skin | 50 (12%) | 10 (6%)
Pruritus | 8 (2%) | 1 (<1%)
Peeling | 9 (2%) | -
Erythema | 6 (1%) | 1 (<1%)
Sunburn | 5 (1%) | -

The actual incidence of dry skin might have been greater were it not for the use of a moisturizer in these studies.

Anaphylaxis, as well as allergic reactions leading to hospitalization, have been reported during post-marketing use of clindamycin/benzoyl peroxide products. Because these reactions are reported voluntarily from a population of uncertain size, it is not always possible to reliably estimate their frequency or establish a causal relationship to drug exposure.

DOSAGE AND ADMINISTRATION

BenzaClin Topical Gel should be applied twice daily, morning and evening, or as directed by a physician, to affected areas after the skin is gently washed, rinsed with warm water and patted dry.

HOW SUPPLIED

BenzaClin Topical Gel is supplied in 6 gram plastic jars (NDC 54868-6062-0).

STORAGE AND HANDLING

Store at room temperature 25°C (77°F).
Do not freeze. Refrigeration is not required. Keep tightly closed. Keep out of the reach of children.

US Patents 5,446,028; 5,767,098
Prescribing Information as of June 2009.

Dermik Laboratories
a business of sanofi-aventis U.S. LLC
Bridgewater, NJ 08807

©2009 sanofi-aventis U.S. LLC

Additional barcode labeling by:
Physicians Total Care, Inc.
Tulsa, OK 74146

PRINCIPAL DISPLAY PANEL - 50g Pump

NDC 54868-6062-0

BenzaClin®
topical gel

clindamycin-benzoyl peroxide gel

FOR TOPICAL USE ONLY

Reconstitute with Clinda–Pak®

One 50g Pump (after reconstitution)